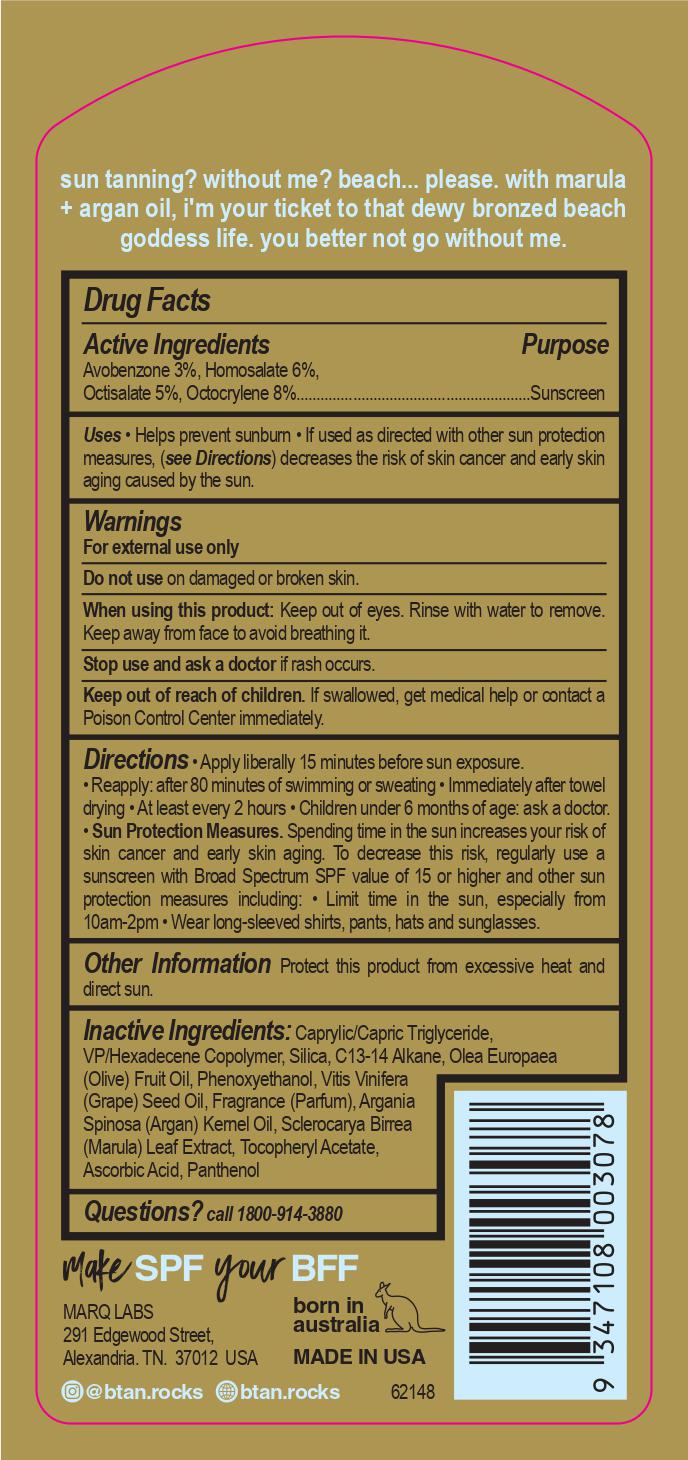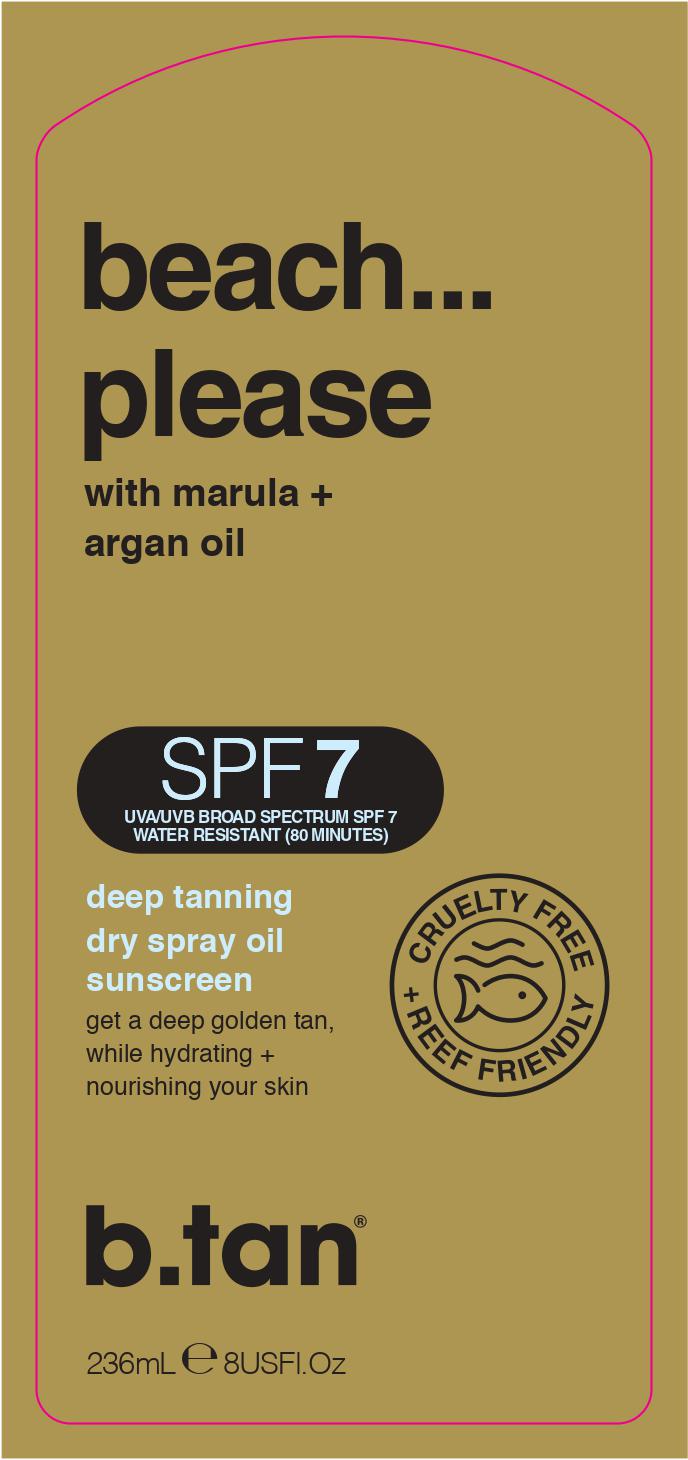 DRUG LABEL: b.tan Beach Please
NDC: 73978-009 | Form: SPRAY
Manufacturer: Marque of Brands Americas, LLC
Category: otc | Type: HUMAN OTC DRUG LABEL
Date: 20251216

ACTIVE INGREDIENTS: AVOBENZONE 3 g/100 mL; HOMOSALATE 6 g/100 mL; OCTISALATE 5 g/100 mL; OCTOCRYLENE 8 g/100 mL
INACTIVE INGREDIENTS: PHENOXYETHANOL; VINYLPYRROLIDONE/HEXADECENE COPOLYMER; TRICAPRIN; GRAPE SEED OIL; PANTHENOL; ALPHA-TOCOPHEROL ACETATE; ASCORBIC ACID; OLIVE OIL; ARGAN OIL; SCLEROCARYA BIRREA SEED OIL; SILICON DIOXIDE; C13-15 ALKANE

b.tan Beach Please SPF 7

ACTIVE INGREDIENT

Avobenzone 3%, Homosalate 6%, Octisalate 5%, Octocrylene 8%

PURPOSE

Sunscreen

INDICATIONS AND USAGE

- Helps prevent sunburn
- If used as directed with other sun protection measures, (see Directions) decreases the risk of skin cancer and early skin aging caused by the sun.

WARNINGS

For external use only

Do not use on damaged or broken skin.

When using this product: Keep out of eyes. Rinse with water to remove. Keep away from face to avoid breathing it.

Stop use and ask a doctor if rash occurs.

Keep out of reach of children. If swallowed, get medical help or contact a Poison Control Center immediately.

Directions

- Apple liberally 15 minutes before sun exposure.
- Reapply: after 80 minutes of swimming or sweating
- Immediately after towel drying
- At least every 2 hours
- Children under 6 months of age: ask a doctor.
- Sun Protection Measures.
- Spending time in the sun increases your risk of skin cancer and early skin aging. To decrease this risk, regularly use a sunscreen Broad Spectrum SPF value of 15 or higher and other sun protection measures including:
- Limit time in the sun, especially from 10am-2pm
- Wear long-sleeved shirts, pants, hats and sunglasses.

OTHER SAFETY INFORMATION

Protect this product from excessive heat and direct sun.

INACTIVE INGREDIENT

Caprylic/Capric Triglyceride, VP/Hexadecene Copolymer, Silica, C13-14 Alkane, Olea Europaea (Olive) Fruit Oil, Phenoxyethanol, Vitis Vinifera (Grape) Seed Oil, Fragrance (Parfum), Argania Spinosa (Argan) Kernel Oil, Sclerocarya Birrea (Marula) Leaf Extract, Tocopheryl Acetate, Ascorbic Acid, Panthenol

QUESTIONS

call 1800-914-3880